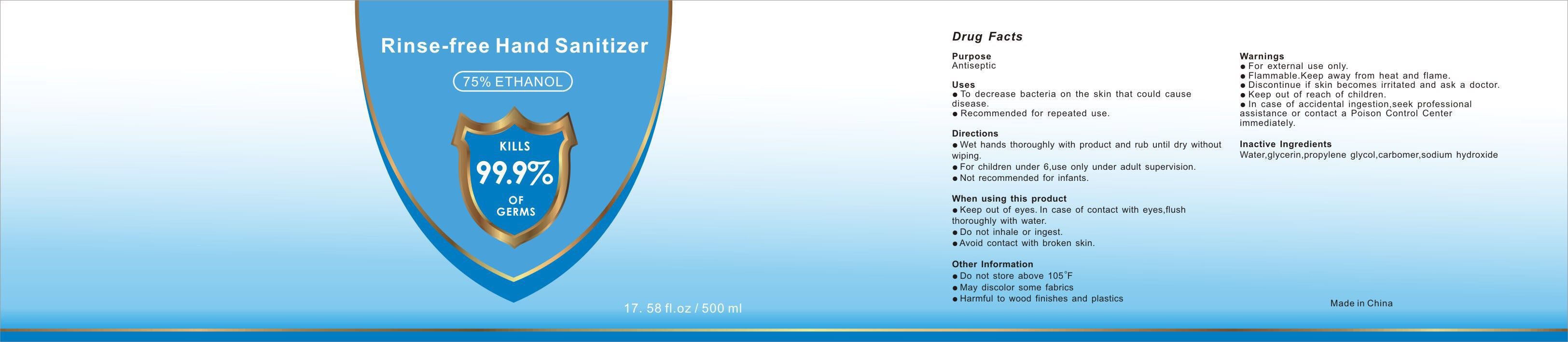 DRUG LABEL: Hand  Sanitizer
NDC: 87269-001 | Form: GEL
Manufacturer: NINGBO MEIDI COSMETICS CO., LTD.
Category: otc | Type: HUMAN OTC DRUG LABEL
Date: 20200610

ACTIVE INGREDIENTS: ALCOHOL 375 mL/500 mL
INACTIVE INGREDIENTS: GLYCERIN; PROPYLENE GLYCOL; TROLAMINE; FD&C BLUE NO. 1; WATER; FD&C YELLOW NO. 5; CARBOMER HOMOPOLYMER, UNSPECIFIED TYPE; D&C RED NO. 33

DOSAGE AND ADMINISTRATION

Do not store above 105 °F

INACTIVE INGREDIENT

aqua，glycerin，propylene glycol，carbomer，triethanolamine，red 33,blue 1,yellow 5

INDICATIONS AND USAGE

Wet hands thoroughly with product and rub until dry without wiping.

ACTIVE INGREDIENT

ethyl alcohol

keep out of reach of children

PURPOSE

Disinfection
Sterilization
No Rinseing

WARNINGS

●For external use only.
●Flammable.Keep away from heat and flame.
●Discontinue if skin becomes irritated and ask a doctor.
●Keep out of reach of children.
●In case of accidental ingestion, seek professional assistance or contact a Poison Control Center immediately.